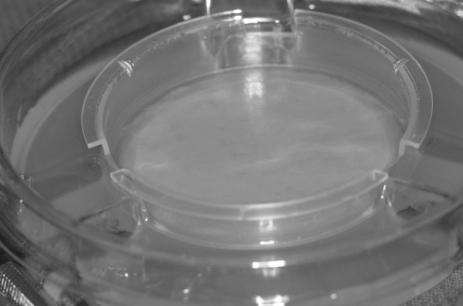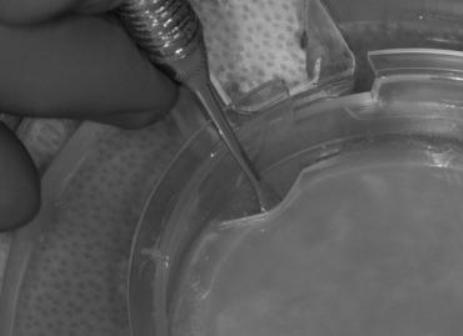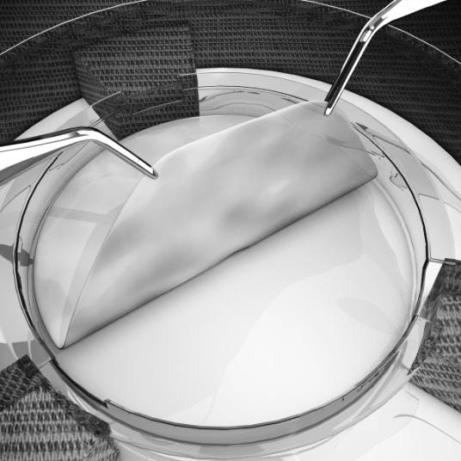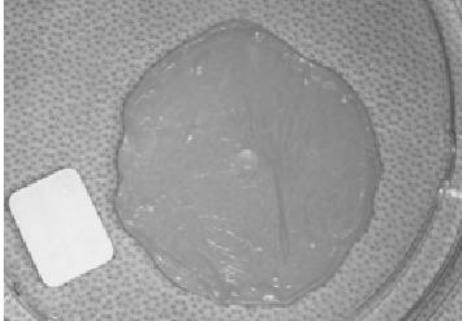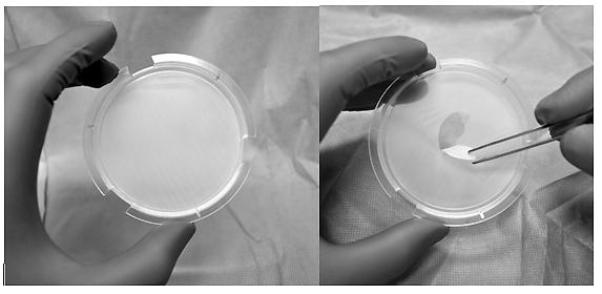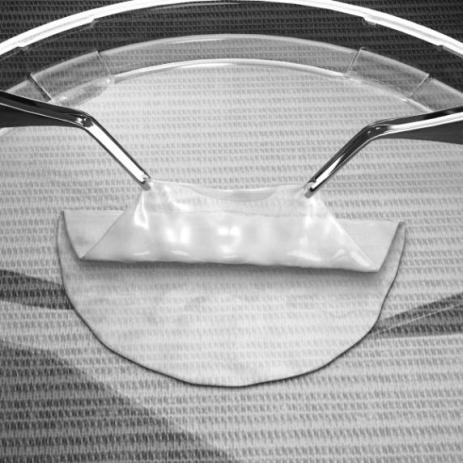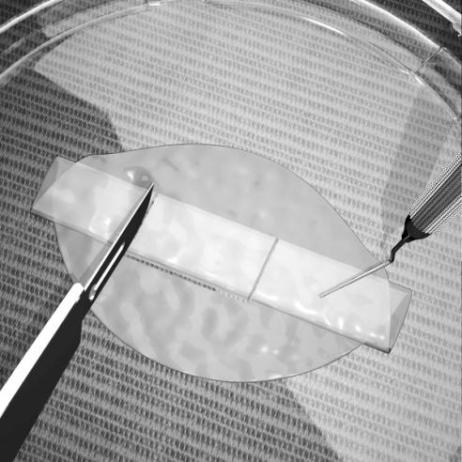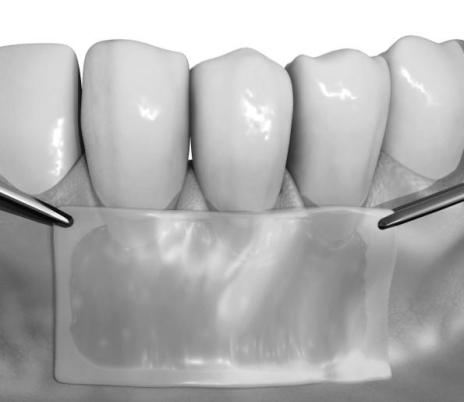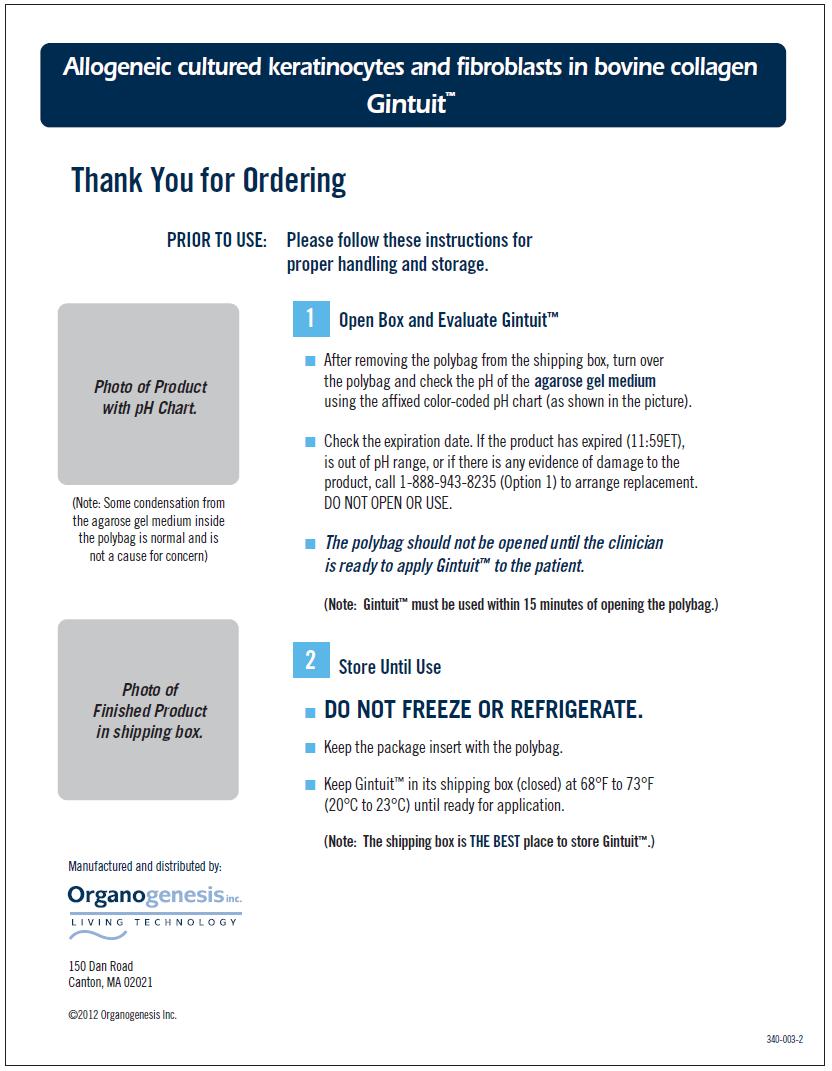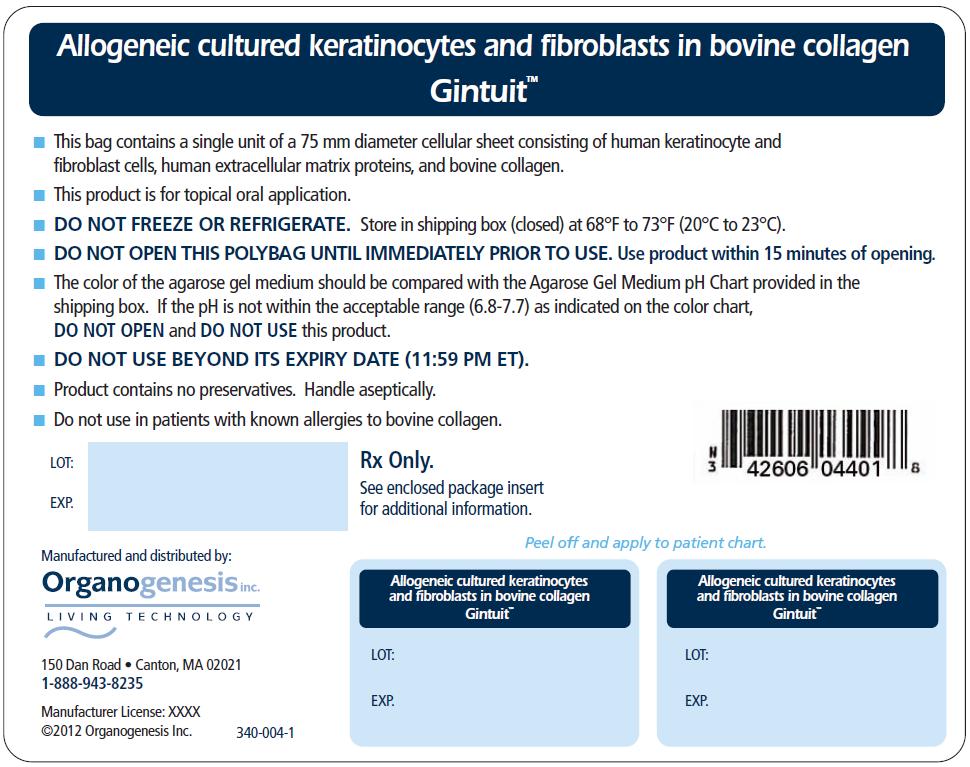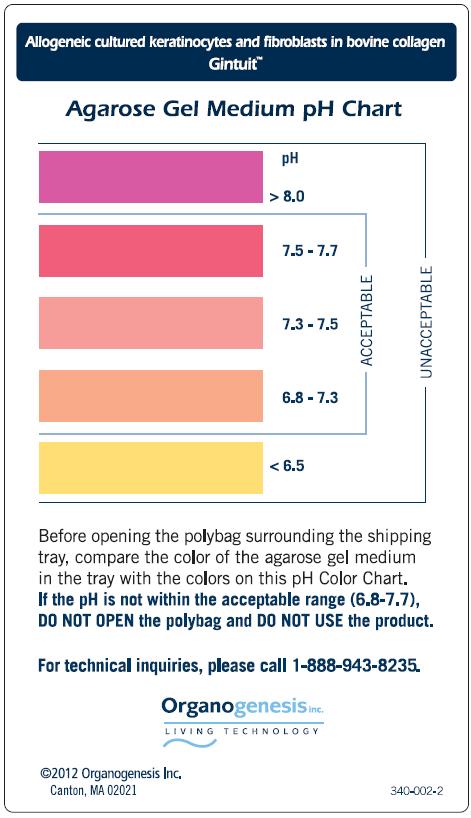 DRUG LABEL: GINTUIT
NDC: 42606-004 | Form: CELLULAR SHEET
Manufacturer: Organogenesis, Inc
Category: other | Type: CELLULAR THERAPY
Date: 20120320

ACTIVE INGREDIENTS: FORESKIN FIBROBLAST (NEONATAL); BOVINE TYPE I COLLAGEN; FORESKIN KERATINOCYTE (NEONATAL)

HIGHLIGHTS OF PRESCRIBING INFORMATION

These highlights do not include all the information needed to use GINTUIT safely and effectively. See full prescribing information for GINTUIT.
GINTUIT (Allogeneic Cultured Keratinocytes and Fibroblasts in Bovine Collagen)
Cellular Sheet for Topical Oral Application
Initial U.S. Approval: 2012

1 INDICATIONS AND USAGE

GINTUIT (Allogeneic Cultured Keratinocytes and Fibroblasts in Bovine Collagen) is an allogeneic cellularized scaffold product indicated for topical (non-submerged) application to a surgically created vascular wound bed in the treatment of mucogingival conditions in adults.

GINTUIT is not intended to provide root coverage.

2 DOSAGE AND ADMINISTRATION

For topical application in the oral cavity only

GINTUIT is used as one application over a surgically created vascular wound bed in the oral cavity. The size of GINTUIT is adjusted for the size of the wound bed. (2.1)

For single patient use only.

The safety and efficacy of repeat application(s) of GINTUIT have not been established. (2.1) (6.1) (14)

3 DOSAGE FORMS AND STRENGTHS

GINTUIT is available as a ready-to-use circular cellular sheet, 75 millimeter (mm) in diameter and approximately 0.75 mm thick, consisting of human keratinocyte and fibroblast cells, human extracellular matrix proteins, and bovine collagen. Approximately 4 million cells are initially used to manufacture the product. (3)

4 CONTRAINDICATIONS

- Oral infection
- Allergy to bovine collagen

GINTUIT is contraindicated for use on clinically infected wounds and in patients with known allergies to bovine collagen or hypersensitivity to the components of the gel medium (agarose). (4)

5 WARNINGS AND PRECAUTIONS

- Hypersensitivity reactions may occur with GINTUIT. (5.1)
- Monitor for signs of wound infection. (5.2)
- The potential for oral cancers is unknown. (5.3)
- Transmission of infectious diseases is a theoretical possibility. (5.4)
- Sterility tests are not completed prior to shipping. (5.5)

6 ADVERSE REACTIONS

The most common adverse reactions observed in the clinical trials (≥1%) included sinusitis, nasopharyngitis, respiratory tract infection, aphthous stomatitis, and the local effects of oral surgery. (6)

To report SUSPECTED ADVERSE REACTIONS, contact Organogenesis Inc. at 1-888-943-8235 or FDA at 1-800-FDA-1088 or www.fda.gov/medwatch.

7 DRUG INTERACTIONS

Topical cytotoxic antiseptics can degrade GINTUIT.

Exposure to topical cytotoxic antibiotics reduces GINTUIT cell viability. (7)

8 USE IN SPECIFIC POPULATIONS

Pregnancy: No human or animal data are available. Use only if clearly needed.

FULL PRESCRIBING INFORMATION

1 INDICATIONS AND USAGE

GINTUIT (Allogeneic Cultured Keratinocytes and Fibroblasts in Bovine Collagen) is an allogeneic cellularized scaffold product indicated for topical (non-submerged) application to a surgically created vascular wound bed in the treatment of mucogingival conditions in adults.

GINTUIT is not intended to provide root coverage.

2 DOSAGE AND ADMINISTRATION

For topical application in the oral cavity only

2.1 Dosage

For single patient use only.

GINTUIT is used as one application over a surgically created vascular wound bed in the oral cavity. The size of GINTUIT is adjusted for the size of the wound bed.

The safety and efficacy of repeat application(s) of GINTUIT have not been established.

2.2 Preparation

Preparation of the Surgical Site

Following local anesthesia, surgically create a vascular wound bed with viable wound edges and establish adequate hemostasis.

Preparation of GINTUIT

- Examine the sealed polybag for any leaks or evidence of damage or contamination.
- Verify the expiration date of GINTUIT. The product expires at 11:59 PM ET on the date of expiration.
- Verify that the product pH (6.8-7.7) is within the acceptable range, using the agarose gel medium pH Color Chart.
- Do not open the polybag until the surgical site has been prepared.
- Use GINTUIT within 15 minutes of opening the sealed polybag.

2.3 Application

- Always handle GINTUIT aseptically.
- Do not use GINTUIT if there is evidence of contamination, visible particulates, or pungent odor.
- GINTUIT, as supplied, is not a biohazardous material; however, follow your local (e.g., institutional or private practice) guidelines for disposal of any remaining GINTUIT.

1. Lift off the tray lid and place it on a surgical sterile field with the outer lid surface facing down. GINTUIT is packaged with the upper layer (containing keratinocytes that appear dull, with a matte finish) facing up and the lower layer (containing fibroblasts in extracellular matrix that appears glossy) facing down, resting on the polycarbonate base attached to the plastic insert (see Figure 1)
  Figure 1:
  GINTUIT, as supplied
2. Using a sterile blunt instrument, gently tease approximately 0.5 inches (1.3 centimeters) of GINTUIT away from the wall of the plastic insert (see Figure 2). Be careful not to perforate or lift the polycarbonate base beneath GINTUIT. The polycarbonate base should remain attached to the plastic insert.
  Figure 2:
  Teasing GINTUIT away from the wall of the plastic insert
3. With sterile gloved hands, insert either one index finger or a sterile blunt instrument under the released section of GINTUIT (see Figure 3). Use another finger or sterile blunt instrument to grasp GINTUIT in a second spot along the edge. Holding GINTUIT in two places, lift the entire GINTUIT out of the plastic insert using a smooth, even motion to prevent GINTUIT from bending and folding over onto itself.
  Figure 3:
  GINTUIT being lifted off the polycarbonate base
4. Place GINTUIT on the inner surface of the tray lid, maintaining the proper orientation (upper layer facing up) (see Figure 4). Handle GINTUIT by its edge to minimize damage.
  Figure 4:
  GINTUIT placed in the inner surface of the upper tray lid
5. Following removal of GINTUIT from the plastic insert, lift the plastic insert that contains the polycarbonate base from the bottom tray to ensure that this base is intact (see Figure 5a - intact polycarbonate base, and Figure 5b - torn polycarbonate base). Verify that pieces of this base are not removed and accidently applied to the patient.
  Figure 5:
  (a) Intact polycarbonate base and (b) torn polycarbonate base
6. Fold GINTUIT into a “z-fold” resulting in the upper layer exposed on the top side and the bottom layer exposed at the bottom side using either sterile gloved hands or sterile blunt instruments (see Figure 6).
  Note: Do not allow GINTUIT to fold or wrinkle upon itself. If needed, add sterile saline or another physiological salt solution to GINTUIT in the tray lid to facilitate folding. Do not use water.
  Figure 6:
  Folding GINTUIT
7. Trim GINTUIT with surgical scissors to the size needed for the surgical site. Use a sterile periodontal probe or other blunt instrument to stabilize the “z-folded” GINTUIT while trimming (see Figure 7).
  Figure 7:
  Trimming GINTUIT
8. Place the lower layer (i.e., fibroblast/extracellular matrix side) of GINTUIT in direct contact with the surgical site so that there are no pockets or wrinkled edges (see Figure 8). If needed, use saline to smooth wrinkles.
  Figure 8:
  Placement of GINTUIT on the surgical wound bed
9. Immobilize and attach GINTUIT to the surgical mucosal defect with sutures placed at the papillae and apically at each corner. If necessary, add a central suture at the apical margin or lateral margins. Use a crisscross (i.e., suspensory or sling) suture over GINTUIT to enhance stability and help maintain direct contact with the wound bed. GINTUIT must not move during mucosal or muscle traction. Tension may cause GINTUIT to tear.
10. If possible, to help protect GINTUIT, place an additional layer of GINTUIT, extending laterally beyond the defect margins over the “z-folded” GINTUIT, and suture at the four corners. The bottom side (i.e., fibroblast/collagen side) of this additional layer should be in contact with the previously applied “z-folded” GINTUIT.
11. Place a non-occlusive protective dressing over the treated site.

3 DOSAGE FORMS AND STRENGTHS

GINTUIT is available as a circular cellular sheet, 75 millimeters (mm) in diameter and approximately 0.75 mm thick, consisting of human keratinocyte and fibroblast cells, human extracellular matrix proteins, and bovine collagen. Approximately 4 million cells are initially used to manufacture the product.

GINTUIT is stored on a semi-permeable polycarbonate base within a plastic insert, which separates the product from an agarose gel medium in a sterile transparent shipping tray.

4 CONTRAINDICATIONS

- Do not use in the presence of oral infection.
- Do not use in patients with known allergies to bovine collagen.

5 WARNINGS AND PRECAUTIONS

Hypersensitivity Reactions

There is a potential for hypersensitivity reactions to occur with GINTUIT.

Monitor for both early and later signs of hypersensitivity reaction following GINTUIT application. Evaluate and treat signs and symptoms of potential allergic reactions according to standard practice. If necessary, remove GINTUIT as part of the treatment for the allergic reaction.

5.2 Wound Infection

Monitor for signs and symptoms of wound infection. Signs of surgical site infection may include pain, edema, erythema, drainage, odor, warmth, or fever. The diagnosis of wound infection may be complicated by the white or yellow appearance of GINTUIT after it becomes hydrated with wound fluid.

5.3 Malignancies

The safety of this product for oral administration has not been evaluated beyond six months. The long-term potential for oral mucosal cancers to arise from, or in response to, this product is unknown.

5.4 Transmission of Infectious Diseases

Transmission of infectious diseases by known or unknown infectious agents may occur with GINTUIT.

GINTUIT contains cells derived from donated human newborn foreskin tissue. The foreskin donor’s mother was tested and found negative for human pathogens, including antibodies to human immunodeficiency virus types 1 and 2 (HIV-1 and HIV-2), human T-lymphotropic virus types 1 and 2 (HTLV-1 and HTLV-2), hepatitis A virus (HAV), hepatitis B virus (HBV), hepatitis B surface antigen (HBsAg), hepatitis C virus (HCV), West Nile virus (WNV), Epstein-Barr virus (EBV), cytomegalovirus (CMV), and syphilis. GINTUIT cells are tested for human and animal viruses, retroviruses, bacteria, fungi, yeast, and mycoplasma.

Product manufacture also includes reagents derived from animal materials, including bovine pituitary extract (BPE). All animal-derived reagents are tested for viruses, retroviruses, bacteria, fungi, yeast, and mycoplasma before use. Bovine materials are sourced to minimize bovine spongiform encephalopathy (BSE), the cause of a rare fatal condition in humans called variant Creutzfeldt-Jakob disease (vCJD). vCJD has never been attributed to use of any medical product manufactured with BPE, but the theoretical possibility cannot be dismissed.

These measures do not totally eliminate the risk of transmitting these or other transmissible infectious diseases and disease agents. Report the occurrence of a transmitted infection to Organogenesis Inc. at 1-888-943-8235.

5.5 Sterility Testing

GINTUIT is shipped after passing primary test results from in-process microbial tests. A final sterility test is initiated prior to shipping, but the result will not be available for up to 14 days. If microbial contamination is detected after the product has been shipped, Organogenesis will notify health care providers and recommend appropriate actions.

6 ADVERSE REACTIONS

The most common adverse reactions observed in the clinical trials (≥1%) included sinusitis, nasopharyngitis, respiratory tract infections, aphthous stomatitis, and the local effects of oral surgery.

6.1 Clinical Trials Experience

Because clinical trials are conducted under widely varying conditions, adverse reaction rates observed in the clinical trials of GINTUIT cannot be directly compared to rates in the clinical trials of another product and may not reflect the rates observed in clinical practice.

GINTUIT has been studied in two randomized, within-subject controlled (i.e., each subject received both GINTUIT and control treatment) clinical studies. The control treatment was a free gingival graft (FGG), using donor graft tissue from the subject’s palate. The duration of the studies was six months following GINTUIT application. Study One was a single-center study (n=25) to evaluate the safety and efficacy of GINTUIT in establishing a zone of attached gingiva. Study Two was a multicenter study (n=96) to evaluate the safety and efficacy of GINTUIT in establishing keratinized tissue (KT) in a similar study population.

Overall, 34% of subjects reported at least one adverse reaction. Table 1 lists all reported adverse reactions that occurred at an incidence of 1% or greater.

Table 1: Adverse Reactions Reported at a Frequency of ≥1% (n=121)*
Reported Adverse Reaction (MedDRA Preferred Term) | Subject n (%) | Events n
OVERALL | 41 (34%) | 65
Sinusitis | 5 (4%) | 6
Nasopharyngitis | 2 (2%) | 2
Respiratory Tract Infection | 2 (2%) | 2
Upper Respiratory Tract Infection | 2 (2%) | 2
Aphthous Stomatitis | 2 (2%) | 2
Oral Pain | 2 (2%) | 2
Mouth Injury | 2 (2%) | 2
Hypoaesthesia Facial | 2 (2%) | 2
* Study One (n=25); Study Two (n=96)

In Studies One and Two, local (occurring at the site of GINTUIT application) adverse reactions included gingival pain, gingival injury (due to inadvertent failure to remove a polycarbonate base from GINTUIT before application), and ulceration.

In another study (n=15), in which the placement of GINTUIT was under a mucosal flap, local (occurring at the site of GINTUIT application) adverse reactions included impaired healing and suture-related complications.

The safety of GINTUIT beyond six months was not evaluated in the clinical trials.

6.2 Postmarketing Experience

GINTUIT is manufactured using a similar process as Apligraf, an FDA-approved medical device. Localized allergic reaction, skin inflammation and erosion, skin blistering, localized wound infection, and cellulitis have been reported during post-approval use of Apligraf for the treatment of chronic cutaneous wounds. Because these reactions are reported voluntarily by a population of uncertain size, and because there are no controls, it is not possible to determine their frequency in the exposed population or establish a causal relationship to exposure to Apligraf. It is uncertain whether information obtained from the postmarketing safety database from use of Apligraf in chronic cutaneous wounds can be extrapolated to use of GINTUIT in the oral environment.

7 DRUG INTERACTIONS

Exposure to topical antiseptics, such as povidone-iodine solution and chlorhexidine (concentrations greater than 0.12%), has been shown to degrade GINTUIT during in vitro and in vivo histological studies.

Exposure to topical antibiotics such as polymyxin/nystatin also reduces GINTUIT cell viability.

If cytotoxic topical antiseptics or antibiotics, including those listed above, have been used, then irrigate the wound thoroughly with saline and allow a suitable wash-out period to elapse before applying GINTUIT.

8 USE IN SPECIFIC POPULATIONS

8.1 Pregnancy

Pregnancy Category C. Animal reproduction studies have not been conducted with GINTUIT. It is also unknown whether GINTUIT can cause fetal harm when administered to a pregnant woman or can affect reproduction capacity. GINTUIT should be used in a pregnant woman only if clearly needed.

8.4 Pediatric Use

The safety and efficacy of GINTUIT in infants and children have not been established.

8.5 Geriatric Use

Clinical studies of GINTUIT did not include sufficient numbers of subjects aged 65 years and older to determine whether they respond differently than younger subjects.

11 DESCRIPTION

GINTUIT, Allogeneic Cultured Keratinocytes and Fibroblasts in Bovine Collagen, is a cellular sheet that contains allogeneic human cells, human extracellular matrix proteins, and bovine collagen for topical application in the oral cavity. GINTUIT appears off-white in color and is comprised of two main layers: an upper cornified layer formed by keratinocytes, and a lower layer constructed of bovine-derived collagen, human extracellular matrix proteins, and dermal fibroblasts. These components interact and produce the final bilayered structure. GINTUIT does not contain Langerhans cells, melanocytes, macrophages, lymphocytes, blood vessels, or hair follicles.

The active ingredients of GINTUIT are the allogeneic keratinocytes, allogeneic dermal fibroblasts, and bovine Type I collagen. In vitro studies have shown that GINTUIT secretes human growth factors and cytokines, and contains extracellular matrix proteins. Growth factors, cytokines, and extracellular matrix proteins are known to be involved in wound repair and regeneration.

The cells are isolated from donated human newborn foreskin tissue and are multiplied into cell banks used in large-scale manufacturing. The donor’s mother is tested and found negative for human pathogens, and the cell banks are extensively tested for microbiological safety [See Warnings and Precautions (5.4)].

Product manufacture also uses reagents derived from animal materials including bovine collagen and bovine pituitary extract (BPE). These reagents are tested for viruses, retroviruses, bacteria, fungi, yeast, and mycoplasma before use.

GINTUIT is shipped in an agarose gel medium to maintain product potency and therefore may contain low amounts of inactive components present from the media. These include agarose Type IV HI EEO, L-glutamine, hydrocortisone, full-chain human recombinant insulin, ethanolamine, O-phosphorylethanolamine, adenine, selenious acid, Dulbecco’s Modified Eagle Medium (DMEM) nutrients, Ham’s F-12 nutrients, sodium bicarbonate, calcium chloride, and water for injection.

A final sterility test is initiated prior to shipping, but the result will not be available for up to 14 days. Passing results from in-process microbial tests are required for release of GINTUIT for shipping.

12 CLINICAL PHARMACOLOGY

12.1 Mechanism of Action

GINTUIT does not function as a tissue graft.

The mechanism of action by which GINTUIT increases keratinized tissue at the treated site has not been identified.

14 CLINICAL STUDIES

The efficacy analysis of GINTUIT was based on two six-month, prospective, randomized, within subject controlled (matched for teeth and gingival condition), treatment comparison clinical trials. A total of 107 subjects from the two trials were included in the efficacy analysis. Each subject received GINTUIT and a free gingival graft (FGG) taken from the subject’s palate (control), with placement sites randomized to two non-adjacent teeth on contralateral sides of the jaw. Treatment of the underlying disease was not addressed in the studies. All subjects completed all study visits in both trials. Subjects in Study One (n=22) were predominantly White (86%) and female (68%), with a mean age of 50 years (range, 31-70). Subjects in Study Two (n=85) were predominantly White (91%) and female (54%), with a mean age of 47 years (range, 18-71).

Study One was a non-inferiority study, conducted at a single center (n=25). The three subjects who participated as training subjects were not included in the efficacy analysis (n=22 for efficacy analysis). The study was designed to rule out a greater than 1 mm decrease in the change in attached gingiva for GINTUIT relative to control. In addition, the amount of keratinized tissue (KT) at the application site was measured. For inclusion, subjects had an insufficient zone of attached gingiva (≤ mm) that required soft tissue grafting. At six months, 14/22 (63.6%) GINTUIT sites and 21/22 (95%) control sites showed an increase in attached gingiva. The mean increase in the amount of attached gingiva was 0.85 mm (95% CI 0.48, 1.21) for GINTUIT and 2.43 mm (95% CI 2.06, 2.79) for control. At least 2 mm of KT width was established in 18/22 (81.8 %) of GINTUIT sites and in 22/22 (100%) of control sites. The mean increase in KT width was 1.37 mm (95% CI 0.97, 1.77) at GINTUIT sites and 3.33 mm (95% CI 2.93, 3.74) at control sites.

Study Two was a multi-center study conducted at four sites in the United States (n = 96). Eleven subjects participated as training subjects and were not included in the efficacy analysis (n=85 for efficacy analysis). The study was designed to determine the percentage of sites with ≥2 mm KT at six months. Eighty-one of the 85 subjects (95.3%) demonstrated ≥2 mm KT at the GINTUIT site (See Table 2). All 96 subjects demonstrated ≥2 mm KT at the control site.

Table 2: Keratinized Tissue ≥2 mm at the GINTUIT site at 6 Months
Month 6 | Statistics | GINTUIT
Subjects with KT width ≥2 mm KT width (mm) | n n (%) 95% CI p- value* Mean (SD) Median Min., Max | 85 81 (95.3%) (88.4, 98.7) <0.001* 3.21 (1.14) 3.0 1.0, 6.0

* Comparison to a pre-defined standard of 50% of subjects with KT width ≥2 mm

In Study Two, GINTUIT sites exhibited superiority for color matching and texture matching (p< 0.0001) and subject preference (p<0.0001) when compared to control.

The effectiveness of GINTUIT beyond six months or with repeat administration was not evaluated in the clinical trials.

16 HOW SUPPLIED/STORAGE AND HANDLING

How Supplied

GINTUIT is supplied ready for use as a cellular sheet approximately 75 mm in diameter and 0.75 mm thick, in a sealed heavy-gauge polyethylene bag (polybag) with a 10% CO2/air atmosphere. GINTUIT is stored on a semi-permeable polycarbonate base within a plastic insert, which separates the product from the agarose gel medium in a sterile transparent shipping tray.
(NDC 42606-044-01)

Storage and Handling

- To maintain cell viability, store GINTUIT in the sealed polybag at 68°F to 73°F (20°C to 23°C) in its shipping box with all insulating components intact until use.
- DO NOT FREEZE OR REFRIGERATE, sterilize, or incubate GINTUIT.
- Inspect the packaging for damage. DO NOT USE GINTUIT if the packaging or seal is damaged.
- Use GINTUIT prior to 11:59 PM ET on the date of expiration printed on the package.

17 PATIENT COUNSELING INFORMATION

Prior to application of GINTUIT, the healthcare provider should

- Discuss the procedure and ask the patient to report any persistent symptoms that occur following the surgical procedure.
- Ask the patient about history of allergy to bovine collagen.

Following application of GINTUIT, provide post-procedure instructions, including the following

- Expect mild to moderate redness, swelling, bruising, or pain following the surgery.
- Do not disturb or disrupt the surgical dressing or GINTUIT. Contact the dental care provider if GINTUIT is dislodged. Leave the post-procedure surgical dressing in place until it falls off on its own, or as instructed by the dental care provider.
- If the dental care provider prescribes a mouth rinse, use it as prescribed and directed. Avoid aggressive rinsing while the dressing is in place.
- Do not brush teeth for the first two weeks after the procedure. After two weeks, resume gentle brushing as directed by the dental care provider. Avoid directly brushing the surgically treated area until instructed by the dental care provider to resume normal brushing.
- Avoid eating hard or rough foods or chewing food on the treated side of the mouth until evaluated by the dental care provider.
- Avoid touching the surgical dressing or treated areas or pulling on the lips or cheek for the first four weeks.
- When directed by the dental care provider, stop using the prescribed rinse and gradually resume normal tooth brushing and flossing.
- Contact the dental care provider if any persistent or unexpected side effects occur.